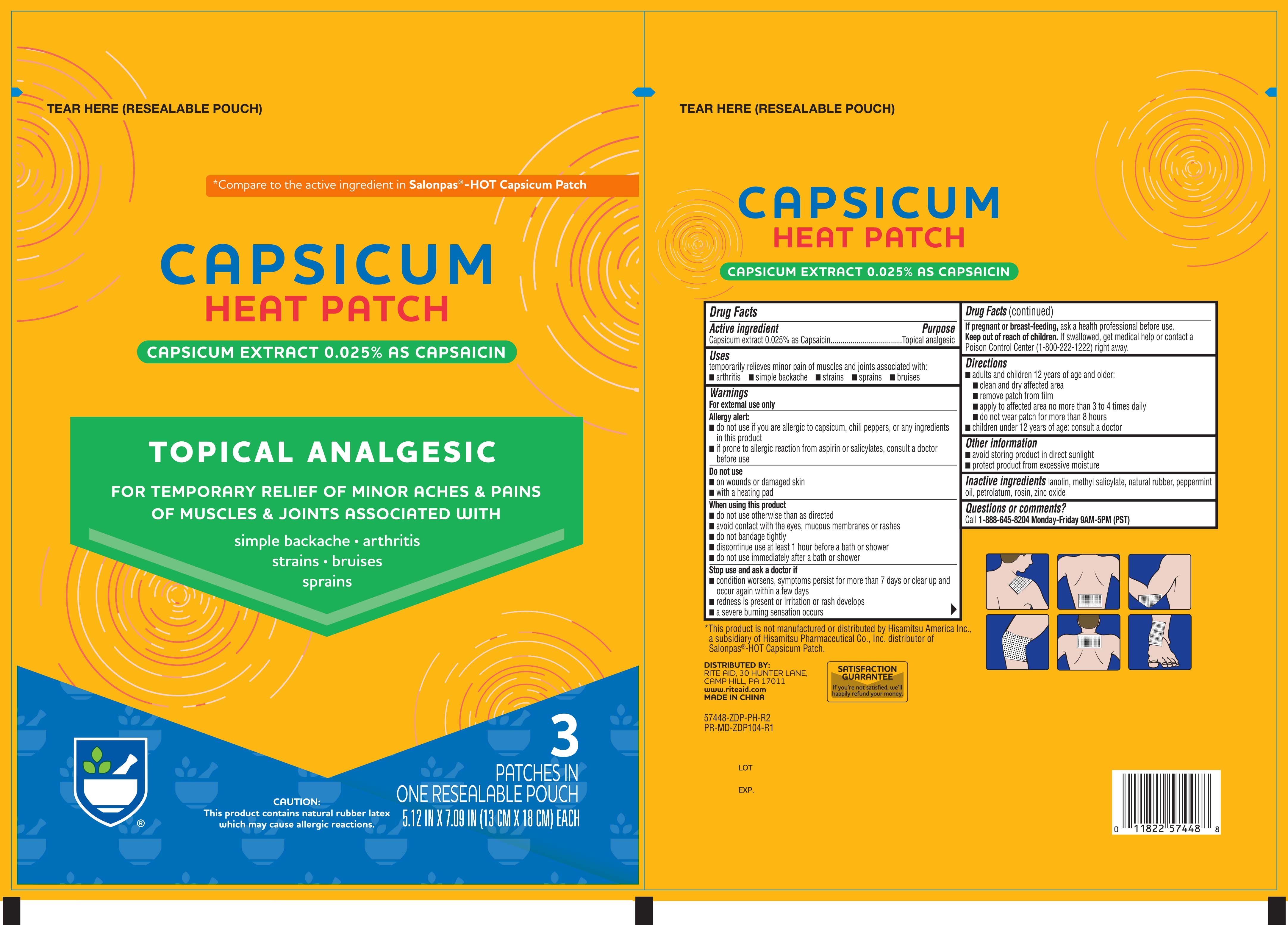 DRUG LABEL: RITE AID CAPSICUM HOT
NDC: 11822-7448 | Form: PATCH
Manufacturer: RITE AID CORPORATION
Category: otc | Type: HUMAN OTC DRUG LABEL
Date: 20220504

ACTIVE INGREDIENTS: CAPSAICIN 0.6 mg/1 1
INACTIVE INGREDIENTS: ZINC OXIDE; LANOLIN; METHYL SALICYLATE; NATURAL LATEX RUBBER; PEPPERMINT OIL; PETROLATUM; ROSIN

Rite-Aid Capsicum Hot Patch 3ct 57448

Active ingredient Purpose

Capsicum extract 0.025% as Capsaicin....................................................................Topical analgesic

Uses

Temporarily relieves minor pain associated with:

- arthritis
- simple backache
- strains
- sprains
- bruises

Warnings

- For external use only
- Allergy alert: Do not use if you are allergic to capsicum, chili peppers, or any ingredients in this product
- if prone to allergic reaction from aspirin or salicylates, consult a doctor before use

Do not use

- on wounds or damaged skin
- with a heating pad

When using this product

- do not use otherwise than as directed
- avoid contact with eyes and mucous membranes or rashes
- do not bandage tightly
- discontinue use at least 1 hour before a bath or shower
- do not use immediately after a bath or shower

Stop use and ask a doctor if

- conditions worsens, symptoms persist more than 7 days or clear up and occur again within a few days
- redness is present or irritation or rash develops
- a severe burning sensation occurs

PREGNANCY OR BREAST FEEDING

If pregnant or breast-feeding, ask a health professional before use.

Keep out of reach of children. If swallowed, get medical help or contact a Poison Control Center right away.

Directions

adults and children 12 years of age and older:

clean and dry affected area

remove patch from film

apply to affected area no more than 3 to 4 times daily

do not wear patch for more than 8 hours

children under 12 years of age: consult a doctor

Other information

- avoid storing product in direct sunlight
- protect product from excessive moisture

Inactive ingredients

lanolin, methyl salicylate, natural rubber, peppermint oil, petrolatum, rosin, zinc oxide

DOSAGE AND ADMINISTRATION

DISTRIBUTED BY:

RITE AID, 30 HUNTER LANE

CAMP HILL, PA 17011

Made in China